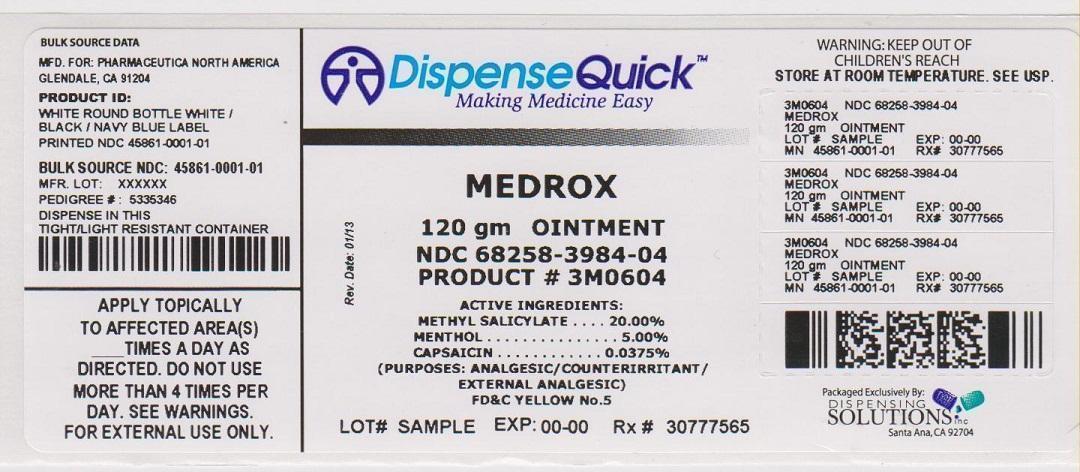 DRUG LABEL: Medrox
NDC: 68258-3984 | Form: OINTMENT
Manufacturer: Dispensing Solutions, Inc.
Category: otc | Type: HUMAN OTC DRUG LABEL
Date: 20130927

ACTIVE INGREDIENTS: METHYL SALICYLATE 20 g/100 g; MENTHOL 5 g/100 g; CAPSAICIN 0.0375 g/100 g
INACTIVE INGREDIENTS: WATER; CETYL ALCOHOL; PEG-150 DISTEARATE; ISOPROPYL MYRISTATE; GLYCERIN; SODIUM LAURYL SULFATE; POLYSORBATE 20; TROLAMINE; PROPYLENE GLYCOL; METHYLPARABEN; PROPYLPARABEN; DIAZOLIDINYL UREA; FD&C BLUE NO. 1; FD&C YELLOW NO. 5

Medrox (Medroxin)

DRUG FACTS:

ACTIVE INGREDIENTS

Methyl Salicylate 20.00%

Menthol 5.00%

Capsaicin 0.0375%

PURPOSE

Analgesic/Counterirritant

Analgesic/Counterirritant

External Analgesic

USES

Use for the temporary relief of minor aches and muscle pains associated with arthritis, simple backache, strains, muscle soreness and stiffness.

WARNINGS

- For external use only. Use only as directed. Avoid contact with eyes and mucous membranes.
- Do not cover with bandage.
- Do not use on wounds or damaged skin.

KEEP OUT OF REACH OF CHILDREN

Consult physician for children under 12.

DIRECTIONS

Apply product directly to affected area. Product may be used as necessary, but should not be used more than four times per day.

OTHER INGREDIENTS

Deionized Water, Cetyl Alcohol, PEG-150 Distearate, Isopropyl Myristate, Glycerin, Sodium Lauryl Sulfate, Polysorbate-20, Triethanolamine, Acrylates Copolymer, Propylene Glycol, Methyl Paraben, Propyl Paraben, Diazolidinyl Urea, FD and C Blue 1, D and C Yellow 5

PACKAGE LABEL.PRINCIPAL DISPLAY PANEL

NDC 68258-3984-04